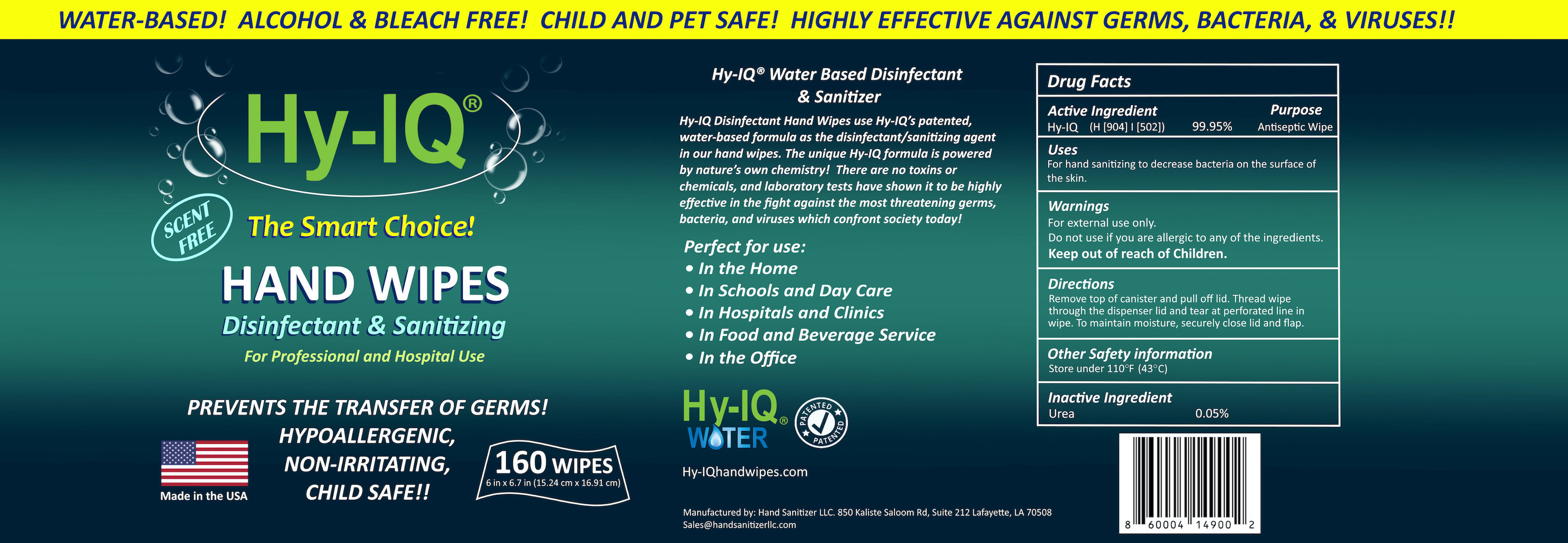 DRUG LABEL: HY-IQ HAND WIPES
NDC: 76701-370 | Form: CLOTH
Manufacturer: Hand Sanitizer LLC
Category: otc | Type: HUMAN OTC DRUG LABEL
Date: 20210617

ACTIVE INGREDIENTS: HYDROGEN CATION 10 mg/1 mL
INACTIVE INGREDIENTS: WATER 940 mg/1 mL; UREA 50 mg/1 mL

ACTIVE INGREDIENT

Hy- IQ Water ([H9O4] | [H5O2])

Hydrogen Cation .77%

PURPOSE

Antiseptic Wipe

INDICATIONS AND USAGE

For hand sanitizing and to help decrease bacteria on the surface of the skin.

WARNINGS

For external use only

Do not use if you are allergic to any of the ingredients.

Stop use and ask a doctor if skin irritation or rash develops right away.

Keep out of reach of children

DOSAGE AND ADMINISTRATION

Directions - remove top of canister and pull off lid. Thread wipe through the dispenser lid and tear at perforated line in wipe. To maintain moisture securely clode lid and flap.

OTHER SAFETY INFORMATION

Store under 110°F (43C)

INACTIVE INGREDIENT

Water, UREA

RECENT MAJOR CHANGES

Product was not used before this date

Hy-IQ Hand Wipes

Hand Disinfecting Wipes